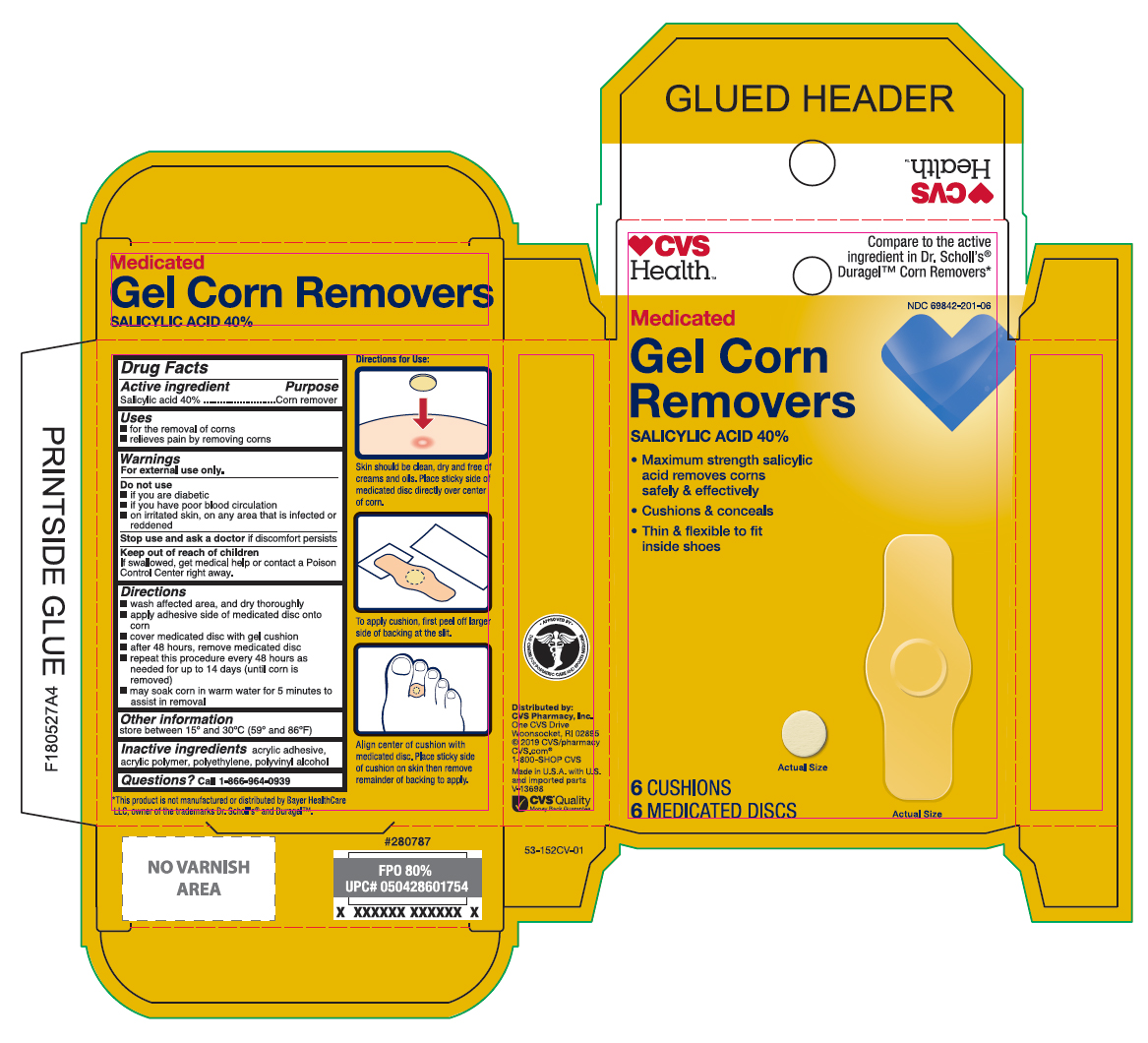 DRUG LABEL: Salicylic Acid
NDC: 69842-201 | Form: PATCH
Manufacturer: CVS Pharmacy
Category: otc | Type: HUMAN OTC DRUG LABEL
Date: 20251223

ACTIVE INGREDIENTS: SALICYLIC ACID 40 mg/6 1
INACTIVE INGREDIENTS: POLYVINYL ALCOHOL, UNSPECIFIED; HIGH DENSITY POLYETHYLENE

CVS Gel Corn Remover

Active Ingredient

Salicylic acid 40%

Purpose

Corn Remover

Uses

- for the removal of corns
- relieves pain by removing corns

Warnings

For external use only.

Do not use

- if you are diabetic
- if you have poor blood circulation
- on irritated skin, on any area that is infected or reddened

Stop use and ask doctor

if discomfort persists

Keep out of reach of children.

If, swallowed, get medical help or contact a Poison Control Center right away.

Directions

- wash affected area and dry thoroughly
- apply adhesive side down of medicated disc on to the corn
- cover the medicated disc with corn cushion
- after 48 hours, remove medicated disc
- repeat this procedure every 48 hours as needed for up to 14 days (until corn is removed)
- may soak corn in warm water for 5 minutes to assist in removal

Other information

store between 15°C to 30°C (59°F to 86°F)

Inactive ingredients

acrylic adhesive, acrylic polymer, polyethylene, polyvinyl alcohol

Questions?

call 1-866-964-0939

Principal Display Panel

CVS Health

Medicated

Gel Corn

Remover

Salicylic Acid 40%

- Maximum strength salicylic

acid removes corns

safely & effectively

- Cushions & conceals
- Thin & flexible to fit

inside shoes

6 CUSHIONS

6 MEDICATED DISCS